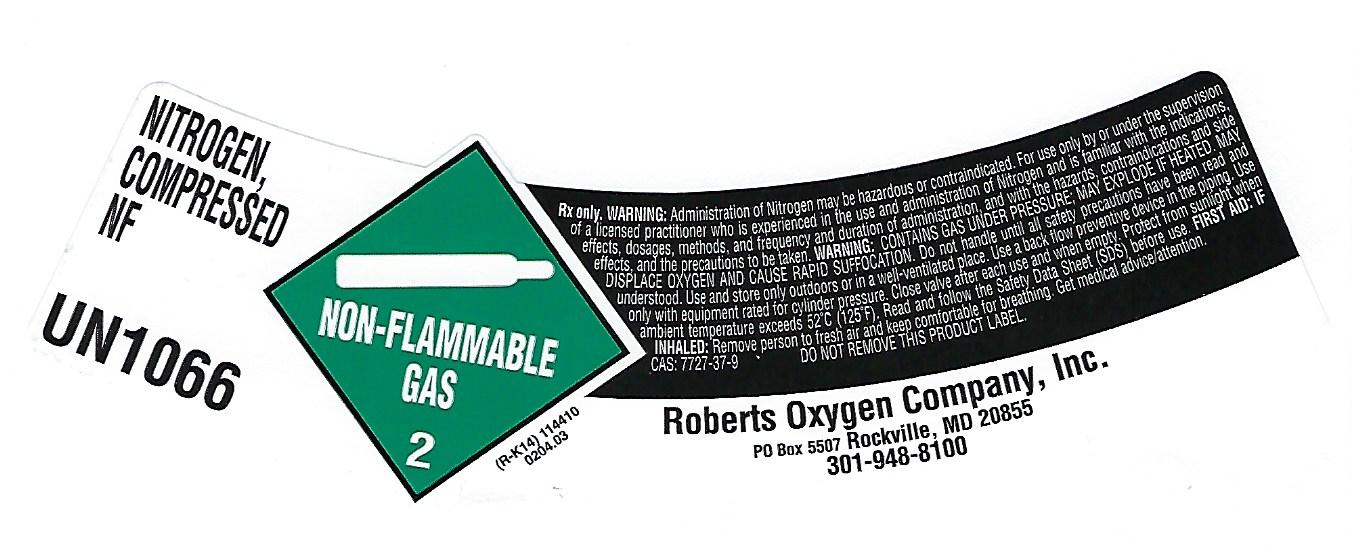 DRUG LABEL: Nitrogen
NDC: 46123-003 | Form: GAS
Manufacturer: Roberts Oxygen Company, Inc
Category: prescription | Type: HUMAN PRESCRIPTION DRUG LABEL
Date: 20251117

ACTIVE INGREDIENTS: NITROGEN 990 mL/1 L

Nitrogen-003

PACKAGE LABEL

NITROGEN,
COMPRESSED
NF
UN1066
NON-FLAMMABLE GAS 2
Rx only. WARNING: Administration of Nitrogen may be hazardous or contraindicated. For use only by or under the supervision of a licensed practitioner who is experienced in the use and administration of nitrogen and is familiar with the indications, effects, dosages, methods, and frequency and duration of administration, and the hazards, contraindications and side effects and the precautions to be taken. WARNING: CONTAINS GAS UNDER PRESSURE; MAY EXPLODE IF HEATED. MAY DISPLACE OXYGEN AND CAUSE RAPID SUFFOCATION. Do not handle until all safety precautions have been read and understood. Use and store only outdoors or in a well-ventilated place. Use a back flow preventative device in the piping. Use only with equipment rated for cylinder pressure. Close valve after each use and when empty. Protect from sunlight when ambient temperature exceeds 52ºC (125ºF). Read and follow the Safety Data Sheet (SDS) before use. FIRST AID: IF INHALED: Remove person to fresh air and keep comfortable for breathing. Get medical advice/attention.
CAS: 7727-37-9 DO NOT REMOVE THIS PRODUCT LABEL
Roberts Oxygen Company, Inc.
PO Box 5507 Rockville, MD 20855
301-948-8100